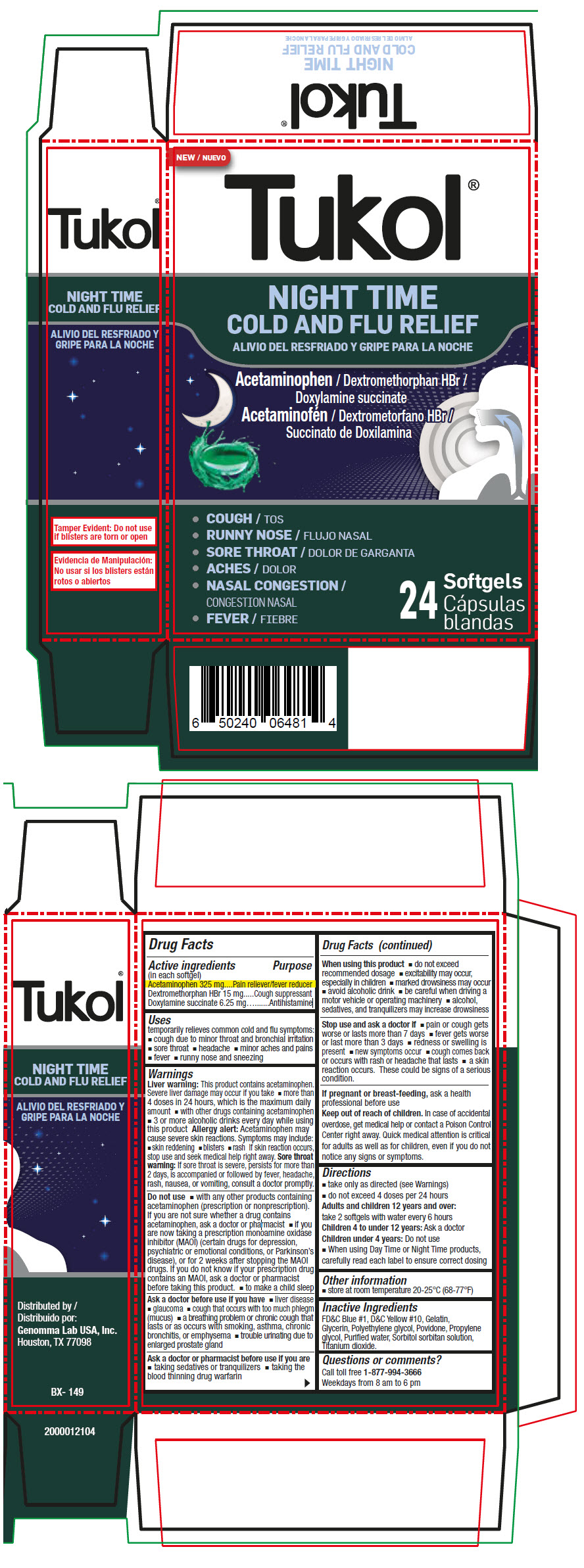 DRUG LABEL: Tukol Night Time Cold and Flu Relief Softgels
NDC: 50066-311 | Form: CAPSULE, LIQUID FILLED
Manufacturer: Genomma Lab USA
Category: otc | Type: HUMAN OTC DRUG LABEL
Date: 20230110

ACTIVE INGREDIENTS: Acetaminophen 325 mg/1 1; Dextromethorphan Hydrobromide 15 mg/1 1; Doxylamine succinate 6.25 mg/1 1
INACTIVE INGREDIENTS: gelatin, unspecified; glycerin; polyethylene glycol, unspecified; povidone, unspecified; propylene glycol; water

Tukol® Night Time Cold and Flu Relief Softgels

Drug Facts

ACTIVE INGREDIENT

Active ingredients (in each softgel) | Purpose
Acetaminophen 325 mg | Pain reliever/fever reducer
Dextromethorphan HBr 15 mg | Cough suppressant
Doxylamine succinate 6.25 mg | Antihistamine

Uses

temporarily relieves common cold and flu symptoms:

- cough due to minor throat and bronchial irritation
- sore throat
- headache
- minor aches and pains
- fever
- runny nose and sneezing

Warnings

Liver warning

This product contains acetaminophen. Severe liver damage may occur if you take

- more than 4 doses in 24 hours, which is the maximum daily amount
- with other drugs containing acetaminophen
- 3 or more alcoholic drinks every day while using this product

Allergy alert

Acetaminophen may cause severe skin reactions. Symptoms may include:

- skin reddening
- blisters
- rash If skin reaction occurs, stop use and seek medical help right away.

Sore throat warning

If sore throat is severe, persists for more than 2 days, is accompanied or followed by fever, headache, rash, nausea, or vomiting, consult a doctor promptly.

Do not use

- with any other products containing acetaminophen (prescription or nonprescription). If you are not sure whether a drug contains acetaminophen, ask a doctor or pharmacist
- if you are now taking a prescription monoamine oxidase inhibitor (MAOI) (certain drugs for depression, psychiatric or emotional conditions, or Parkinson's disease), or for 2 weeks after stopping the MAOI drugs. If you do not know if your prescription drug contains an MAOI, ask a doctor or pharmacist before taking this product.
- to make a child sleep

Ask a doctor before use if you have

- liver disease
- glaucoma
- cough that occurs with too much phlegm (mucus)
- a breathing problem or chronic cough that lasts or as occurs with smoking, asthma, chronic bronchitis, or emphysema
- trouble urinating due to enlarged prostate gland

Ask a doctor or pharmacist before use if you are

- taking sedatives or tranquilizers
- taking the blood thinning drug warfarin

When using this product

- do not exceed recommended dosage
- excitability may occur, especially in children
- marked drowsiness may occur
- avoid alcoholic drink
- be careful when driving a motor vehicle or operating machinery
- alcohol, sedatives, and tranquilizers may increase drowsiness

Stop use and ask a doctor if

- pain or cough gets worse or lasts more than 7 days
- fever gets worse or last more than 3 days
- redness or swelling is present
- new symptoms occur
- cough comes back or occurs with rash or headache that lasts
- a skin reaction occurs. These could be signs of a serious condition.

PREGNANCY OR BREAST FEEDING

If pregnant or breast-feeding, ask a health professional before use

Keep out of reach of children. In case of accidental overdose, get medical help or contact a Poison Control Center right away. Quick medical attention is critical for adults as well as for children, even if you do not notice any signs or symptoms.

Directions

- take only as directed (see Warnings)
- do not exceed 4 doses per 24 hours
  Adults and children 12 years and over: take 2 softgels with water every 6 hours
  Children 4 to under 12 years: Ask a doctor
  Children under 4 years: Do not use
- When using Day Time or Night Time products, carefully read each label to ensure correct dosing

Other information

- store at room temperature 20-25°C (68-77°F)

Inactive Ingredients

FD&C Blue #1, D&C Yellow #10, Gelatin, Glycerin, Polyethylene glycol, Povidone, Propylene glycol, Purified water, Sorbitol sorbitan solution, Titanium dioxide.

Questions or comments?

Call toll free 1-877-994-3666

Weekdays from 8 am to 6 pm

Distributed by
Genomma Lab USA, Inc.
Houston, TX 77098

PRINCIPAL DISPLAY PANEL - 24 Softgel Blister Pack Carton

NEW

Tukol®

NIGHT TIME
COLD AND FLU RELIEF

Acetaminophen / Dextromethorphan HBr /
Doxylamine succinate

◆ COUGH
◆ RUNNY NOSE
◆ SORE THROAT
◆ ACHES
◆ NASAL CONGESTION
◆ FEVER

24
Softgels